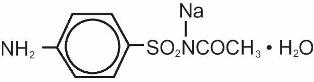 DRUG LABEL: Unknown
Manufacturer: Alcon
Category: prescription | Type: Human Prescription Drug Label
Date: 20061120

DESCRIPTION

ISOPTO CETAMIDE® (sulfacetamide sodium ophthalmic solution USP) 15% and CETAMIDE™ (sulfacetamide sodium ophthalmic ointment, USP) 10% are sterile topical antibacterial agents for ophthalmic use. The active ingredient is represented by the following structural formula:

Chemical name: N-Sulfanilylacetamide monosodium salt monohydrate.

Each mL of solution contains: Active: Sulfacetamide sodium 15% (150 mg/mL). Preservative: Methylparaben 0.05%, Propylparaben 0.01%. Vehicle: 0.5% Hydroxyporpyl Methylcellulose 2910 (viscosity type, 4000 cps). Inactive: Sodium Thiosulfate 0.3%, Dibasic Sodium Phosphate and/or Monobasic Sodium Phosphate (to adjust pH), Purified Water.

pH range between 7.0 and 7.8 DM-02

Each gram of ointment contains: Active: Sulfacetamide Sodium 10% (100 mg). Preservatives: Methylparaben 0.05%, Propylparaben 0.01%. Inactive: White Petrolatum, Anhydrous Liquid Lanolin, Mineral Oil. DM-00

CLINICAL PHARMACOLOGY

Microbiology

The sulfonamides are bacteriostatic agents and the spectrum of activity is similar for all. Sulfonamides inhibit bacterial synthesis of dihydrofolic acid by preventing the condensation of the pteridine with aminobenzoic acid through competitive inhibition of the enzyme dihydropteroate synthetase. Resistant strains have altered dihydropteroate synthetase with reduced affinity for sulfonamides or produce increased quantities of aminobenzoic acid.

Topically applied sulfonamides are considered active against susceptible strains of the following common bacterial eye pathogens: Escherichia coli, Staphylococcus aureus, Streptococcus pneumoniae, Streptococcus (viridans group), Haemophilus influenzae, Klebsiella species, and Enterobacter species.

Topically applied sulfonamides do not provide adequate coverage against Neisseria species, Serratia marcescens and Pseudomonas aeruginosa. A significant percentage of Staphylococcal isolates are completely resistant to sulfa drugs.

INDICATIONS AND USAGE

Solution

For the treatment of conjunctivitis and other superficial ocular infections due to susceptible microorganisms and as an adjunctive in systemic sulfonamide therapy of trachoma: Escherichia coli, Staphylococcus aureus, Streptococcus pneumoniae, Streptococcus (viridans group), Haemophilus influenzae, Klebsiella species, and Enterobacter species.

Ointment

For the treatment of conjunctivitis and other superficial ocular infections due to susceptible microorganisms. Topically applied sulfonamides do not provide adequate coverage against Neisseria species, Serratia marcescens and Pseudomonas aeruginosa. A significant percentage of staphylococcal isolates are completely resistant to sulfa drugs.

CONTRAINDICATIONS

Hypersensitivity to sulfonamides or to any ingredient of the preparation.

WARNINGS

FOR TOPICAL EYE USE ONLY – NOT FOR INJECTION. FATALITIES HAVE OCCURRED, ALTHOUGH RARELY, DUE TO SEVERE REACTIONS TO SULFONAMIDES INCLUDING STEVENS-JOHNSON SYNDROME, TOXIC EPIDERMAL NECROLYSIS, FULMINANT HEPATIC NECROSIS, AGRANULOCYTOSIS, APLASTIC ANEMIA AND OTHER BLOOD DYSCRASIAS. Sensitizations may recur when a sulfonamide is readministered, irrespective of the route of administration. Sensitivity reactions have been reported in individuals with no prior history of sulfonamide hypersensitivity. At the first sign of hypersensitivity, skin rash or other serious reaction, discontinue use of this preparation.

PRECAUTIONS

General

Prolonged use of topical anti-bacterial agents may give rise to overgrowth of nonsusceptible organisms including fungi. Bacterial resistance to sulfonamides may also develop. Ophthalmic ointments may retard corneal wound healing. The effectiveness of sulfonamides may be reduced by the para-aminobenzoic acid present in purulent exudates. Sensitization may recur when a sulfonamide is readministered irrespective of the route of administration, and cross-sensitivity between different sulfonamides may occur. At the first sign of hypersensitivity, increase in purulent discharge, or aggravation of inflammation or pain, the patient should discontinue use of the medication and consult a physician (see WARNINGS).

Information for Patients

To avoid contamination, do not touch tip of container to eye, eyelid or any surface.

Drug Interactions

Sulfacetamide preparations are incompatible with silver preparations.

Carcinogenesis, Mutagenesis, Impairment of Fertility

No studies have been conducted in animals or in humans to evaluate the possibility of these effects with ocularly administered sulfacetamide. Rats appear to be especially susceptible to the goitrogenic effects of sulfonamides, and long-term oral administration of sulfonamides has resulted in thyroid malignancies in these animals.

Pregnancy

Pregnancy Category C. Animal reproduction studies have not been conducted with sulfonamide ophthalmic preparations. Kernicterus may occur in the newborn as a result of treatment of a pregnant woman at term with orally administered sulfonamides. This product should be used in pregnancy only if the potential benefit justifies the potential risk to the fetus.

Nursing Mothers

Systemically administered sulfonamides are capable of producing kernicterus in infants of lactating women. Because of the potential for the development of kernicterus in neonates, a decision should be made whether to discontinue nursing or discontinue the drug taking into account the importance of the drug to the mother.

Pediatric Use

Safety and effectiveness in pediatric patients below the age of two months have not been established.

ADVERSE REACTIONS

Bacterial and fungal corneal ulcers have developed during treatment with sulfonamide ophthalmic preparations. The most frequently reported reactions are local irritation, stinging and burning. Less commonly reported reactions include non-specific conjunctivitis, conjunctival hyperemia, secondary infections and allergic reactions. Fatalities have occurred, although rarely, due to severe reactions to sulfonamides including Stevens-Johnson syndrome, toxic epidermal necrolysis, fulminant hepatic necrosis, agranulocytosis, aplastic anemia, and other blood dyscrasias (see WARNINGS).

DOSAGE AND ADMINISTRATION

For conjunctivitis and other superficial ocular infections:

Solution: Instill one or two drops into the conjunctival sac(s) of the affected eye(s) every two to three hours initially. Dosages may be tapered by increasing the time interval between doses as the condition responds. The usual duration of treatment is seven to ten days.

Ointment: Apply a small amount (approximately one-half inch ribbon) into the conjunctival sac(s) of the affected eye(s) every three to four hours and at bedtime. Dosages may be tapered by increasing the time interval between doses as the condition responds. The ointment may be used as adjunct to the solution. The usual duration of treatment is seven to ten days.

How to apply CETAMIDE™ Ointment:

1. Tilt your head back.
2. Place a finger on your cheek just under your eye and gently pull down until a “V” pocket is formed between your eyeball and your lower lid.
3. Place a small amount (about ½ inch) of CETAMIDE™ Ointment in the “V” pocket. Do not let the tip of the tube touch your eye.
4. Look downward before closing your eye.

For Trachoma:

Solution: Instill two drops into the conjunctival sac(s) of the affected eye(s) every two hours. Topical administration must be accompanied by systemic administration.

HOW SUPPLIED

Solution in 5mL and 15mL plastic DROP-TAINER® Dispensers. Ointment in 3.5g ophthalmic tubes:

5 mL solution - NDC 0998-0522-05

15 mL solution - NDC 0998-0522-15

3.5 g ointment - NDC 0065-0526-35

STORAGE

Solution – Store at 8° - 24°C (46° - 75°F). Protect from light. Do not use if solution is discolored (dark brown). Sulfonamide solutions, on long standing, will darken in color and should be discarded.

Ointment – Store at 8° - 27°C (46°-80°F).

CAUTION: Federal (USA) law prohibits dispensing without prescription.

341035

Rev: January 1995

Alcon®

OPHTHALMIC

ALCON LABORATORIES, INC.

Fort Worth, TX 76134 USA

Printed in USA